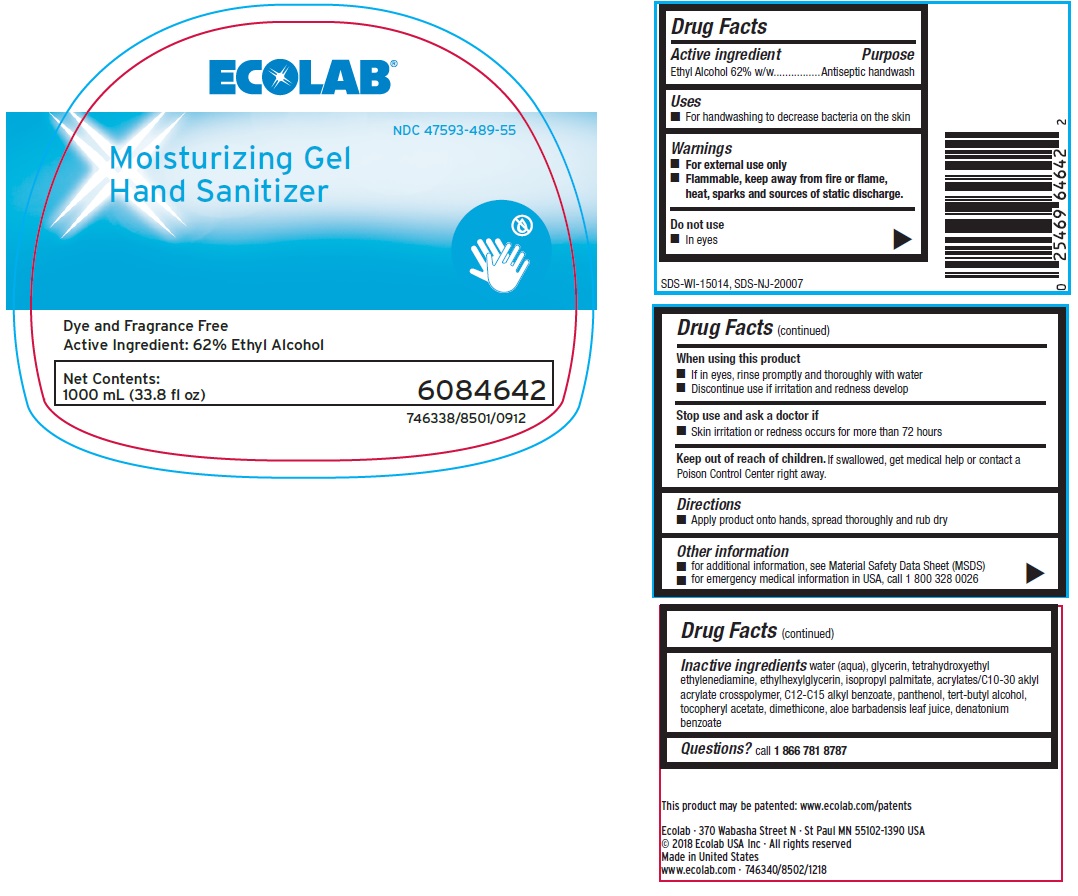 DRUG LABEL: Ecolab
NDC: 47593-489 | Form: SOLUTION
Manufacturer: Ecolab Inc.
Category: otc | Type: HUMAN OTC DRUG LABEL
Date: 20240426

ACTIVE INGREDIENTS: ALCOHOL 620 mg/1 mL
INACTIVE INGREDIENTS: WATER; GLYCERIN; ETHYLENEDIAMINE TETRAETHANOL; ETHYLHEXYLGLYCERIN; ISOPROPYL PALMITATE; CARBOMER INTERPOLYMER TYPE A (ALLYL SUCROSE CROSSLINKED); ALKYL (C12-15) BENZOATE; PANTHENOL; TERT-BUTYL ALCOHOL; .ALPHA.-TOCOPHEROL ACETATE; DIMETHICONE; ALOE VERA LEAF; DENATONIUM BENZOATE

Drug Facts

Active Ingredient

Ethyl Alcohol 62% w/w

Purpose

Antiseptic handwash

Uses

- For handwashing to decrease bacteria on the skin

Warnings

- For external use only
- Flammable, keep away from fire or flame, heat, sparts and sources of static discharge.

Do not use

- In eyes

When using this product

- If in eyes, rinse promptly and thoroughly with water
- Discontinue use if irritation and redness develop

Stop use and ask doctor if

- Skin irritation or redness persists for more than 72 hours

Keep out of reach of children. If swallowed, get medical help or contact a Poison Control Center right away.

Directions

- Apply product onto hands, spread thoroughly and rub dry

Other information

- for additional information, see Material Safety Data Sheet (MSDS)
- for emergency medical information in USA and Canada, call 1 800 328 0026

INACTIVE INGREDIENT

Inactive ingredients water (aqua), glycerin, tetrahydroxyethyl ethylenediamine, ethylhexylglycerin, isopropyl palmitate, acrylates/C10-30 alkyl acrylate crosspolymer, C12-C15 alkyl benzoate, panthenol, tert-butyl alcohol, tocopheryl acetate, dimethicone, aloe barbadensis leaf juice, denatonium benzoate

Questions? call 1 866 781 8787

Representative Label and Principal Display Panel

ECOLAB®

NDC 47593-489-55

Moisturizing Gel

Hand Sanitizer

Dye and Fragrance Free

Active Ingredient: 62% Ethyl Alcohol

Net Contents: 6084642

1000 mL (33.8 fl oz)

746338/8501/0912

Ecolab · 370 Wabasha Street N · St Paul MN 55102-1390 USA

© 2018 Ecolab USA Inc · All rights reserved

Made in United States

746340/8502/1218